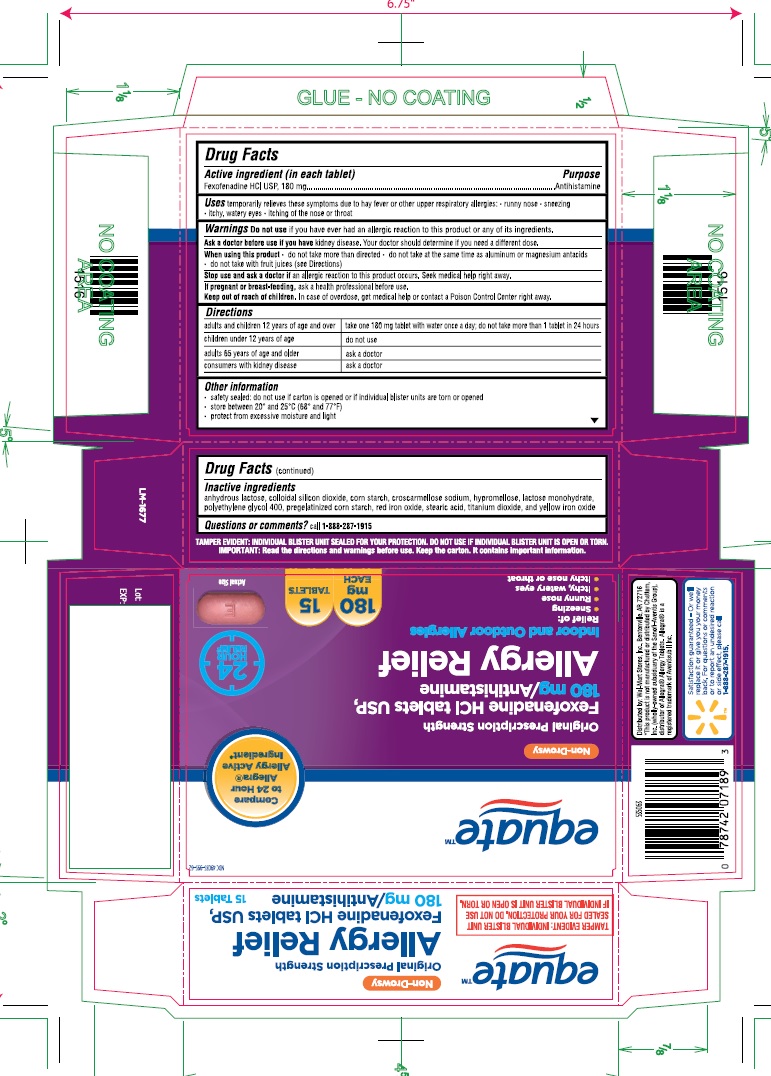 DRUG LABEL: Fexofenadine hydrochloride
NDC: 49035-995 | Form: TABLET, FILM COATED
Manufacturer: Wal-Mart Stores, Inc
Category: otc | Type: Human OTC Drug Label
Date: 20190911

ACTIVE INGREDIENTS: FEXOFENADINE HYDROCHLORIDE 180 mg/1 1
INACTIVE INGREDIENTS: ANHYDROUS LACTOSE; SILICON DIOXIDE; STARCH, CORN; CROSCARMELLOSE SODIUM; HYPROMELLOSES; LACTOSE MONOHYDRATE; POLYETHYLENE GLYCOL 400; FERRIC OXIDE RED; STEARIC ACID; TITANIUM DIOXIDE; FERRIC OXIDE YELLOW

ACTIVE INGREDIENT(S)

Fexofenadine HCl USP, 180 mg

PURPOSE

Antihistamine

USE(S)

temporarily relieves these symptoms due to hay fever or other upper respiratory allergies:

- runny nose
- sneezing
- itchy, watery eyes
- itching of the nose or throat

WARNINGS

Do not use if you have ever had an allergic reaction to this product or any of its ingredients.

ASK A DOCTOR BEFORE USE IF

you have kidney disease. Your doctor should determine if you need a different dose.

WHEN USING THIS PRODUCT

- do not take more than directed
- do not take at the same time as aluminium or magnesium antacids
- do not take with fruit juices (see Directions)

STOP USE AND ASK DOCTOR IF

an allergic reaction to this product occurs. Seek medical help right away.

IF PREGNANT OR BREAST-FEEDING

ask a health professional before use.

KEEP OUT OF REACH OF CHILDREN

In case of overdose, get medical help or contact a Poison Control Center right away.

DIRECTIONS

adults and children 12 years of age and over | take one 180 mg tablet with water once a day; do not take more than 1 tablet in 24 hours
children under 12 years of age | do not use
adults 65 years of age and older | ask a doctor
consumers with kidney disease | ask a doctor

OTHER INFORMATION

- safety sealed: do not use if carton is opened or if individual blister units are torn or opened
- store between 20^0 and 25^0C (68^0 and 77^0F)
- protect from excessive moisture and light

INACTIVE INGREDIENTS

anhydrous lactose, colloidal silicon dioxide, corn starch,croscarmellose sodium, hypromellose, lactose monohydrate, polyethylene glycol 400, pregelatinized corn starch, red iron oxide, stearic acid, titanium dioxide, and yellow iron oxide

QUESTIONS OR COMMENTS?

call 1-888-287-1915

PRINCIPAL DISPLAY PANEL

NDC 49035-995-62
Non-Drowsy
Original Prescription Strength
Fexofenadine HCl Tablets USP,
180 mg/Antihistamine
Allergy Relief
Indoor and Outdoor Allergies
Relief of:

- Sneezing
- Runny nose
- Itchy, watery eyes
- Itchy nose or throat 180 mg EACH 15 TABLETS